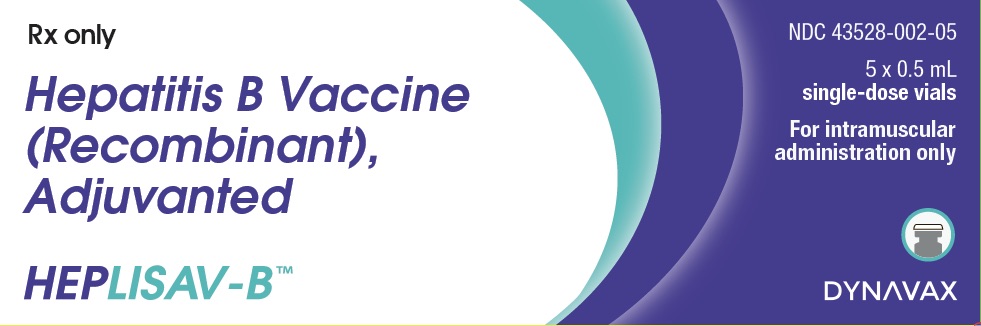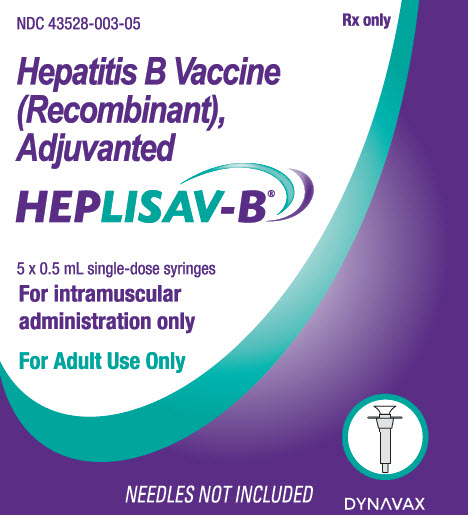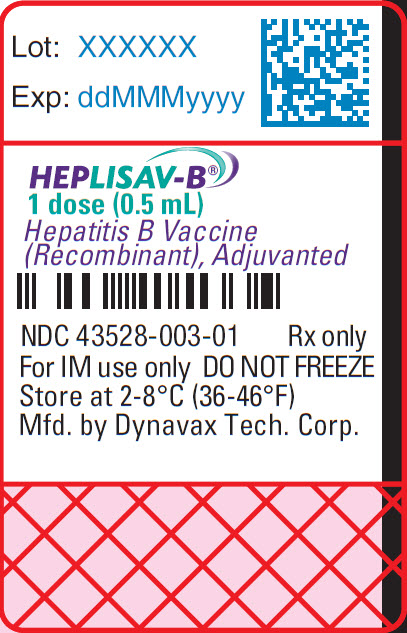 DRUG LABEL: HEPLISAV-B
NDC: 43528-002 | Form: INJECTION, SOLUTION
Manufacturer: Dynavax Technologies Corporation
Category: other | Type: VACCINE LABEL
Date: 20260219

ACTIVE INGREDIENTS: HEPATITIS B VIRUS SUBTYPE ADW HBSAG SURFACE PROTEIN ANTIGEN 20 ug/0.5 mL
INACTIVE INGREDIENTS: 1018 ISS; SODIUM CHLORIDE; SODIUM PHOSPHATE, DIBASIC, DODECAHYDRATE; SODIUM PHOSPHATE, MONOBASIC, DIHYDRATE; POLYSORBATE 80; WATER

HIGHLIGHTS OF PRESCRIBING INFORMATION

These highlights do not include all the information needed to use HEPLISAV-B®safely and effectively. See full prescribing information for HEPLISAV-B.
HEPLISAV-B [Hepatitis B Vaccine (Recombinant), Adjuvanted] injection, for intramuscular use
Initial U.S. Approval: 2017

1 INDICATIONS AND USAGE

HEPLISAV-B is indicated for prevention of infection caused by all known subtypes of hepatitis B virus. HEPLISAV-B is approved for use in adults 18 years of age and older. (1)

2 DOSAGE AND ADMINISTRATION

For intramuscular use.
Administer a series of 2 doses (0.5-mL each) at the following schedule: 0, 1 month. (2.1, 2.2)

3 DOSAGE FORMS AND STRENGTHS

HEPLISAV-B is an injection. A single dose of HEPLISAV-B is 0.5 mL. (3)

4 CONTRAINDICATIONS

Severe allergic reaction, such as anaphylaxis, after a previous dose of any hepatitis B vaccine or to any component of HEPLISAV-B, including yeast. (4)

6 ADVERSE REACTIONS

The most common local reaction was injection site pain (9% - 39%). The most common systemic reactions were fatigue (10% - 17%) and headache (5% - 17%). (6.1)

To report SUSPECTED ADVERSE REACTIONS, contact Dynavax at 1-844-889-8753 or VAERS at 1-800-822-7967 and www.vaers.hhs.gov.

FULL PRESCRIBING INFORMATION

1 INDICATIONS AND USAGE

HEPLISAV-B is indicated for prevention of infection caused by all known subtypes of hepatitis B virus. HEPLISAV-B is approved for use in adults 18 years of age and older.

2 DOSAGE AND ADMINISTRATION

For intramuscular use.

2.1 Dose and Regimen

Administer intramuscularly as a series of 2 doses (0.5-mL dose each) at the following schedule: 0, 1 month.

2.2 Administration

HEPLISAV-B is a clear to slightly opalescent, colorless to slightly yellow solution.

Parenteral drug products should be inspected visually for particulate matter and discoloration prior to administration, whenever solution and container permit. If either of these conditions exists, the vaccine should not be administered.

Administer HEPLISAV-B by intramuscular injection in the deltoid region using a sterile needle and syringe.

3 DOSAGE FORMS AND STRENGTHS

HEPLISAV-B is an injection.
A single dose of HEPLISAV-B is 0.5 mL.

4 CONTRAINDICATIONS

Do not administer HEPLISAV-B to individuals with a history of severe allergic reaction (e.g. anaphylaxis) after a previous dose of any hepatitis B vaccine or to any component of HEPLISAV-B, including yeast [see Description(11)].

5 WARNINGS AND PRECAUTIONS

5.1 Managing Allergic Reactions

Appropriate medical treatment and supervision must be available to manage possible anaphylactic reactions following administration of HEPLISAV-B.

5.2 Immunocompromised Individuals

Immunocompromised persons, including individuals receiving immunosuppressant therapy, may have a diminished immune response to HEPLISAV-B.

5.3 Limitations of Vaccine Effectiveness

Hepatitis B has a long incubation period. HEPLISAV-B may not prevent hepatitis B infection in individuals who have an unrecognized hepatitis B infection at the time of vaccine administration.

6 ADVERSE REACTIONS

6.1 Clinical Trials Experience

Because clinical trials are conducted under widely varying conditions, adverse reaction rates observed in the clinical trials of a vaccine cannot be directly compared to rates in the clinical trials of another vaccine and may not reflect the rates observed in practice.

A total of 9597 individuals 18 through 70 years of age received at least 1 dose of HEPLISAV-B in 5 clinical trials conducted in the United States, Canada, and Germany. Data from 3 of these trials are provided below.

Study 1 in Subjects 18 through 55 Years of Age

Study 1 was a randomized, observer-blind, active-controlled, multicenter study in Canada and Germany in which 1810 subjects received at least 1 dose of HEPLISAV-B and 605 subjects received at least 1 dose of Engerix-B®[Hepatitis B Vaccine (Recombinant)]. Enrolled subjects had no history of hepatitis B vaccination or infection. HEPLISAV-B was given as a 2-dose regimen at 0 and 1 month followed by saline placebo at 6 months. Engerix-B was given at 0, 1, and 6 months. In the total study population, the mean age was 40 years; 46% of the subjects were men; 93% were white, 2% black, 3% Asian and 3% Hispanic; 26% were obese, 10% had hypertension, 8% had dyslipidemia, and 2% had diabetes mellitus. These demographic and baseline characteristics were similar in both vaccine groups.

Solicited Local and Systemic Adverse Reactions
Subjects were monitored for local and systemic adverse reactions using diary cards for a 7-day period starting on the day of vaccination. The percentages of subjects who reported local and systemic reactions are shown in Table 1.

 | Table 1 Study 1: Percent of Subjects Who Reported Local or Systemic Reactions Within 7 Days of Vaccination
 | HEPLISAV-B % |  | Engerix-B %
 | Post-Dose [HEPLISAV-B was given as a 2-dose regimen at 0 and 1 month followed by saline placebo at 6 months. Engerix-B was given at 0, 1, and 6 months] |  | Post-Dose
Reaction | 1 | 2 | 1 | 2 | 3
Local | N=1810 | N=1798 | N=605 | N=603 | N=598
Injection Site Pain | 38.5 | 34.8 | 33.6 | 24.7 | 20.2
Injection Site Redness [Redness and swelling ≥ 2.5 cm.] | 4.1 | 2.9 | 0.5 | 1.0 | 0.7
Injection Site Swelling | 2.3 | 1.5 | 0.7 | 0.5 | 0.5
Systemic
Fatigue | 17.4 | 13.8 | 16.7 | 11.9 | 10.0
Headache | 16.9 | 12.8 | 19.2 | 12.3 | 9.5
Malaise | 9.2 | 7.6 | 8.9 | 6.5 | 6.4
 | N=1784 | N=1764 | N=596 | N=590 | N=561
Fever [Oral temperature ≥ 100.4°F (38.0°C).] | 1.1 | 1.5 | 1.8 | 1.7 | 1.8
Note: only subjects having data are included. Clinical trial number: NCT00435812

Unsolicited Adverse Events:
Unsolicited adverse events within 28 days following any injection, including placebo, were reported by 42.0% of HEPLISAV-B recipients and 41.3% of Engerix-B recipients.

Serious Adverse Events (SAEs)
Subjects were monitored for serious adverse events for 7 months after the first dose of vaccine. The percentage of subjects reporting serious adverse events was 1.5% in the HEPLISAV-B group and 2.1% in the Engerix-B group. No acute myocardial infarctions were reported. No deaths were reported.

Potentially Immune-mediated Adverse Events
Potentially immune-mediated adverse events that occurred within 7 months of the first dose of vaccine were reported in 0.2% (n = 4) of HEPLISAV-B recipients and 0.7% (n = 4) of Engerix-B recipients. The following events were reported in the HEPLISAV-B group in one subject each: granulomatosis with polyangiitis, lichen planus, Guillain-Barré syndrome, and Grave’s disease. The following events were reported in the Engerix-B group in one subject each: Bell’s palsy, Raynaud’s phenomenon, and Grave’s disease. One additional Engerix-B recipient with a history of mixed connective tissue disease had p- ANCA-positive vasculitis.

Study 2 in Subjects 40 through 70 Years of Age

Study 2 was a randomized, observer-blind, active-controlled, multicenter study in Canada and the United States in which 1968 subjects received at least 1 dose of HEPLISAV-B and 481 subjects received at least 1 dose of Engerix-B. HEPLISAV-B was given as a 2-dose regimen at 0 and 1 month followed by saline placebo at 6 months. Enrolled subjects had no history of hepatitis B vaccination or infection. Engerix-B was given at 0, 1, and 6 months. In the total population, the mean age was 54 years; 48% of subjects were men; 82% were white, 15% black, 1% Asian and 6% Hispanic; 44% were obese, 30% had hypertension, 30% had dyslipidemia, and 8% had diabetes mellitus. These demographic and baseline characteristics were similar in both vaccine groups.

Solicited Local and Systemic Adverse Reactions
Subjects were monitored for local and systemic adverse reactions using diary cards for a 7-day period starting on the day of vaccination. The percentages of subjects who experienced local and systemic reactions are shown in Table 2.

 | Table 2 Study 2: Percent of Subjects Who Reported Local or Systemic Reactions Within 7 Days of Vaccination
 | HEPLISAV-B % |  | Engerix-B %
 | Post-Dose [HEPLISAV-B was given as a 2-dose regimen at 0 and 1 month followed by saline placebo at 6 months. Engerix-B was given at 0, 1, and 6 months] |  | Post-Dose
Reaction | 1 | 2 | 1 | 2 | 3
Local | N=1952 | N=1905 | N=477 | N=464 | N=448
Injection Site Pain | 23.7 | 22.8 | 18.4 | 15.9 | 13.8
Injection Site Redness [Redness and swelling ≥ 2.5 cm] | 0.9 | 0.7 | 0.6 | 0.2 | 0.2
Injection Site Swelling | 0.9 | 0.6 | 0.6 | 0.6 | 0.2
Systemic
Fatigue | 12.6 | 10.8 | 12.8 | 12.1 | 9.4
Headache | 11.8 | 8.1 | 11.9 | 9.5 | 8.5
Malaise | 7.7 | 7.0 | 8.6 | 7.1 | 5.1
Myalgia | 8.5 | 6.4 | 9.6 | 8.0 | 4.5
 | N=1923 | N=1887 | N=472 | N=459 | N=438
Fever [Oral temperature ≥ 100.4°F (38.0°C).] | 0.6 | 0.6 | 0.6 | 0.9 | 0.7
Note: only subjects having data are included. Clinical Trial Number: NCT01005407

Unsolicited Adverse Events:
Unsolicited adverse events within 28 days following any injection, including placebo, were reported by 35.4% of HEPLISAV-B recipients and 36.2% of Engerix-B recipients.

Serious Adverse Events
Subjects were monitored for serious adverse events for 12 months after the first dose of vaccine. The percentage of subjects reporting serious adverse events was 3.9% in the HEPLISAV-B group and 4.8% in the Engerix-B group. Acute myocardial infarction occurred in 0.1% (n=2) of HEPLISAV-B recipients and 0.2% (n=1) of Engerix-B recipients.

Autoimmune Adverse Events
Subjects were monitored for the occurrence of new-onset potentially immune-mediated adverse events for 12 months after the first dose of vaccine. Events were adjudicated as to whether they were autoimmune by an external group of experts blinded to treatment assignment. As determined by the adjudicators, new-onset autoimmune adverse events were reported in 0.2% (n=3) of HEPLISAV-B recipients: two subjects with hypothyroidism and one subject with vitiligo. None of these events was considered related to vaccination by the expert group. No new-onset autoimmune adverse events were reported in the Engerix-B group. Although not referred to the external group of experts, one HEPLISAV-B recipient was determined to have Tolosa-Hunt syndrome which is presumed to have an immune-mediated etiology. This event was not considered related to vaccination.

Deaths
One subject (0.05%) died of a pulmonary embolism in the HEPLISAV-B group and 1 subject (0.2%) died of heart failure in the Engerix-B group. Neither death was considered related to vaccination.

Study 3 in Subjects 18 through 70 Years of Age

Study 3 was a randomized, observer-blind, active-controlled, multicenter study in the United States in which 5587 subjects received at least 1 dose of HEPLISAV-B and 2781 subjects received at least 1 dose of Engerix-B. Enrolled subjects had no history of hepatitis B vaccination or infection. HEPLISAV-B was given as a 2-dose regimen at 0 and 1 month followed by saline placebo at 6 months. Engerix-B was given at 0, 1, and 6 months. In the total study population, the mean age was 50 years; 51% were men; 71% were white, 26% black, 1% Asian, and 9% Hispanic; 48% were obese, 36% had hypertension, 32% had dyslipidemia, and 14% had type 2 diabetes mellitus. These demographic and baseline characteristics were similar in both vaccine groups.

Unsolicited Medically-Attended Adverse Events
Subjects were monitored for unsolicited medically-attended adverse events, those for which a subject sought medical care, for 13 months after the first dose of vaccine. Overall, medically-attended adverse events were reported in 46.0% of HEPLISAV-B recipients and 46.2% of Engerix-B recipients. Herpes zoster was reported in 0.7% of HEPLISAV-B recipients and 0.3% of Engerix-B recipients. Unsolicited medically-attended adverse events within 28 days following any injection, including placebo, were reported by 20.1% of both HEPLISAV-B and Engerix-B recipients.

Serious Adverse Events
Subjects were monitored for serious adverse events for 13 months after the first dose of vaccine. The percentage of subjects who reported serious adverse events was 6.2% in the HEPLISAV-B group and 5.3% in the Engerix-B group. Acute myocardial infarction (AMI) was reported in 0.25% (n=14) of HEPLISAV-B recipients and 0.04% (n=1) of Engerix-B recipients. An analysis of serious adverse events likely representing myocardial infarction (MI) was conducted using the standard Medical Dictionary for Regulatory Activities (MedDRA) query (SMQ) for MI. This analysis identified a total of 19 HEPLISAV-B subjects (0.3%) and 3 Engerix-B subjects (0.1%) with events included in the SMQ for MI (these events include the 15 reports of AMI). Additional evidence, including information on temporal relationship and baseline risk factors, does not support a causal relationship between HEPLISAV-B administration and AMI. Among the 19 events identified as MI in HEPLISAV-B recipients, three occurred within 14 days, nine occurred within 53-180 days, and seven occurred more than 180 days following any dose of HEPLISAV-B. Among the three events identified as MI in Engerix- B recipients, one each occurred 13, 115, and 203 days following any dose. All 19 HEPLISAV-B recipients and 3 Engerix-B recipients reported one or more baseline risk factors for cardiovascular disease.

Autoimmune Adverse Events
Subjects were monitored for the occurrence of new-onset potentially immune-mediated adverse events for 13 months after the first dose of vaccine. Events were adjudicated as to whether they were autoimmune by an external group of experts who were blinded to treatment assignment. As determined by the adjudicators, new-onset autoimmune adverse events were reported in 0.1% (n=4) of HEPLISAV-B recipients [one each of: alopecia areata, polymyalgia rheumatica, ulcerative colitis, and autoimmune thyroiditis (with concurrent diagnosis of papillary thyroid carcinoma)]. None of these events was considered to be related to vaccination by the external experts. No new-onset autoimmune adverse events were reported in the Engerix-B group.

Deaths
During the study death was reported in 25 subjects (0.4%) in the HEPLISAV-B group and 7 subjects (0.3%) in the Engerix-B group. No death was considered related to vaccination.

6.2 Postmarketing Experience

The following adverse reactions have been identified during post-approval use of HEPLISAV-B. Because these reactions are reported voluntarily from a population of uncertain size, it is not always possible to reliably estimate their frequency or establish a causal relationship to vaccine exposure.

Immune System Disorders
Anaphylaxis and other hypersensitivity reactions including urticaria, pruritus, and rash.

Nervous System Disorders
Dizziness, paresthesia

Gastrointestinal Disorders
Gastrointestinal symptoms including nausea, vomiting, diarrhea, and abdominal pain

General Disorders and Administration Site Conditions
Injection site pruritus

7 DRUG INTERACTIONS

7.1 Use with Immune Globulin

There are no data to assess the concomitant use of HEPLISAV-B with immune globulin. When concomitant administration of HEPLISAV-B and immune globulin is required, they should be given with different syringes at different injection sites.

7.2 Interference with Laboratory Tests

Hepatitis B surface antigen (HBsAg) derived from hepatitis B vaccines has been transiently detected in blood samples following vaccination. Serum HBsAg detection may not have diagnostic value within 28 days after receipt of HEPLISAV-B.

8 USE IN SPECIFIC POPULATIONS

8.1 Pregnancy

Pregnancy Exposure Registry

Risk Summary

All pregnancies have a risk of birth defect, loss, or other adverse outcomes. In clinically recognized pregnancies in the US general population, the estimated background risk of major birth defects is 2% to 4% and of miscarriage is 15% to 20%.

There are no adequate and well-controlled studies of HEPLISAV-B in pregnant individuals. Available data, primarily in individuals who received one dose of HEPLISAV-B in the 28 days prior to or during pregnancy, do not suggest an increased risk of major birth defects and miscarriage [see Data].

In a developmental toxicity study, 0.3 mL of a vaccine formulation containing 2.5 mcg HBsAg and 3000 mcg cytidine phospho-guanosine (CpG) 1018 adjuvant (A full human dose of HEPLISAV-B contains 20 mcg HBsAg and 3000 mcg CpG 1018 adjuvant) was administered to female rats prior to mating and during gestation. This animal study revealed no evidence of harm to the fetus due to this vaccine formulation [see Data].

Data

Human data

A post-licensure observational retrospective cohort study included 81 individuals who were exposed to HEPLISAV-B during the 28 days prior to conception or during pregnancy. The estimated date of conception was determined based on available data for estimated date of delivery, date of last menstrual period, or gestational age from ultrasound measurements. After excluding elective terminations (n=1) and those with unknown birth outcomes (n=5), there were 75 pregnancies with known outcomes. Of the 75 pregnancies, 10 were in individuals who received HEPLISAV-B twice during the period from 28 days prior to conception through the end of pregnancy. Among 75 recipients with exposure to HEPLISAV-B that occurred prior to or during pregnancy: 44 received HEPLISAV-B during the 28 days prior to conception, 24 during the first trimester, 6 during the second trimester, and 1 during the third trimester. Of 73 individuals exposed to HEPLISAV-B during the 28 days prior to conception through the first 20 weeks of gestation, 6 individuals (8.2%) had a miscarriage (4 were in individuals exposed once, and 2 were in individuals exposed twice). One individual exposed to HEPLISAV-B in the second trimester had a stillbirth. No major birth defects were observed. These data, primarily in individuals who received one dose of HEPLISAV-B, do not suggest an increased risk of major birth defects and miscarriage.

Animal Data

A developmental toxicity study was conducted in female rats. Animals were administered 0.3 mL of a vaccine formulation containing 2.5 mcg HBsAg and 3000 mcg CpG 1018 adjuvant twice prior to mating, and on gestation days 6 and 18 (a full human dose of HEPLISAV-B contains 20 mcg HBsAg and 3000 mcg CpG 1018 adjuvant). No adverse effects on female fertility, pre-natal and post-natal development up to the time of weaning were observed. There were no vaccine-related fetal malformations or variations observed. During the postweaning development observation period the reproductive capacity of the male and female F1 generation was evaluated; no adverse effects on mating and fertility of F1 litters were observed.

8.2 Lactation

Risk Summary

It is not known whether HEPLISAV-B is excreted in human milk. Data are not available to assess the effects of HEPLISAV-B on the breastfed infant or on milk production/excretion.

The developmental and health benefits of breastfeeding should be considered along with the mother’s clinical need for HEPLISAV-B and any potential adverse effects on the breastfed child from HEPLISAV- B or from the underlying maternal condition. For preventive vaccines, the underlying condition is susceptibility to disease prevented by the vaccine.

8.4 Pediatric Use

Safety and effectiveness of HEPLISAV-B have not been established in individuals less than 18 years of age.

8.5 Geriatric Use

Clinical trials included 909 adults 65 through 70 years of age who received HEPLISAV-B.

Among subjects who received HEPLISAV-B, a seroprotective level of antibody to HBsAg was achieved in 90% of those 65 through 70 years of age compared to 96% of those aged 18 through 64 years of age.

Safety and effectiveness of HEPLISAV-B in adults older than 70 years of age were extrapolated from findings in subjects younger than 70 years of age.

8.6 Adults on Hemodialysis

Safety and effectiveness of HEPLISAV-B have not been established in adults on hemodialysis.

11 DESCRIPTION

HEPLISAV-B [Hepatitis B Vaccine (Recombinant), Adjuvanted] is an injection for intramuscular use.

The HBsAg is expressed in a recombinant strain of Hansenula polymorphayeast. The fermentation process involves growth of the recombinant H. polymorphaon chemically-defined fermentation media containing vitamins and mineral salts.

The HBsAg is expressed intra-cellularly in the yeast cells. It is released from the yeast cells by cell disruption and purified by a series of physicochemical steps. Each dose may contain residual amounts of yeast protein (≤5.0% of total protein), yeast DNA (<20 picogram), and deoxycholate (<0.9 ppm) from the HBsAg manufacturing process.

HEPLISAV-B is prepared by combining the purified HBsAg together with the CpG 1018 adjuvant, a 22-mer phosphorothioate linked oligodeoxynucleotide in a phosphate buffered saline (sodium chloride, 9.0 mg/mL; sodium phosphate, dibasic dodecahydrate, 1.75 mg/mL; sodium phosphate, monobasic dihydrate, 0.48 mg/mL; and polysorbate 80, 0.1 mg/mL).

Each 0.5-mL dose is formulated to contain 20 mcg of HBsAg and 3000 mcg of CpG 1018 adjuvant.

HEPLISAV-B is available in prefilled syringes. The tip caps and stoppers of the prefilled syringes are not made with natural rubber latex.

HEPLISAV-B is formulated without preservatives. [see How Supplied/Storage and Handling(16)].

12 CLINICAL PHARMACOLOGY

12.1 Mechanism of Action

Infection with hepatitis B virus can have serious consequences including acute massive hepatic necrosis and chronic active hepatitis. Chronically infected persons are at increased risk for cirrhosis and hepatocellular carcinoma.

Antibody concentrations ≥10 mIU/mL against HBsAg are recognized as conferring protection against hepatitis B virus infection.

13 NONCLINICAL TOXICOLOGY

13.1 Carcinogenesis, Mutagenesis, Impairment of Fertility

HEPLISAV-B has not been evaluated for carcinogenicity, mutagenic potential.

14 CLINICAL STUDIES

14.1 Evaluation of Seroprotection

The immunogenicity of HEPLISAV-B was evaluated in comparison with a licensed hepatitis B vaccine (Engerix-B) in 3 randomized, active controlled, observer-blinded, multi-center Phase 3 clinical trials of adults. HEPLISAV-B was given as a 2-dose regimen at 0 and 1 months followed by saline placebo at 6 months. Engerix-B was given at 0, 1, and 6 months.

The trials compared the seroprotection rates (% with antibody concentration ≥ 10 mIU/mL) induced by HEPLISAV-B and Engerix-B. Noninferiority was met if the lower bound of the 95% confidence interval of the difference in seroprotection rates (HEPLISAV-B minus Engerix-B) was greater than -10%.

Study 1: Seroprotection in Adults 18 through 55 Years of Age
In Study 1, the immunogenicity population comprised 1511 participants who received HEPLISAV-B and 521 who received Engerix-B. The mean age was 40 years for both groups. The primary analysis compared the seroprotection rate at Week 12 for HEPLISAV-B with that at Week 28 for Engerix-B. Non-inferiority of the seroprotection rate induced by HEPLISAV-B compared to Engerix-B was demonstrated (Table 3).

 | Table 3 Study 1: Seroprotection Rate of HEPLISAV-B and Engerix-B (ages 18 through 55 years)
Timepoint | HEPLISAV-B N = 1511 | Engerix-B N = 521 | Difference in SPRs (HEPLISAV-B minus Engerix-B)
 | SPR (95% CI) | SPR (95% CI) | Difference (95% CI)
Week 12 (HEPLISAV-B) Week 28 (Engerix-B) | 95% (93.9, 96.1) | 81.3% (77.8, 84.6) | 13.7% (10.4, 17.5) [Noninferiority was met because the lower bound of the 95% confidence interval of the difference in SPRs was greater than -10%.]
CI = confidence interval; N = number of subjects in the analysis population in the group; SPR = seroprotection rate (% with anti-HBs ≥ 10 mIU/mL).
Clinical trial number: NCT00435812

Study 2: Seroprotection in Adults 40 through 70 Years of Age
In Study 2, the immunogenicity population comprised 1121 subjects who received HEPLISAV-B and 353 subjects who received Engerix-B. The mean age was 54 years for both groups. The primary analysis compared the seroprotection rate at Week 12 for HEPLISAV-B with that at Week 32 for Engerix-B. Non- inferiority of the seroprotection rate induced by HEPLISAV-B compared to Engerix-B was demonstrated (Table 4).

 | Table 4 Study 2: Seroprotection Rate of HEPLISAV-B and Engerix-B (ages 40 through 70 years)
Timepoint | HEPLISAV-B N = 1121 | Engerix-B N = 353 | Difference in SPRs (HEPLISAV-B minus Engerix-B)
 | SPR (95% CI) | SPR (95% CI) | Difference (95% CI)
Week 12 (HEPLISAV-B) Week 32 (Engerix-B) | 90.1% (88.2, 91.8) | 70.5% (65.5, 75.2) | 19.6% (14.7, 24.8) [Noninferiority was met because the lower bound of the 95% confidence interval of the difference in SPRs was greater than -10%.]
CI = confidence interval; N = number of subjects in the analysis population in the group; SPR = seroprotection rate (% with anti-HBs ≥ 10 mIU/mL).
The SPR following HEPLISAV-B was statistically significantly higher than following Engerix-B (lower bound of the 95% confidence interval of the difference in SPRs was greater than 0%).
Clinical trial number: NCT01005407

Study 3: Seroprotection in Adults 18 through 70 Years of Age Including those with Type 2 Diabetes Mellitus
In Study 3, the immunogenicity population comprised 4537 subjects who received HEPLISAV-B and 2289 subjects who received Engerix-B. The mean age was 51 years and 14% of subjects had type 2 diabetes mellitus (defined as having a clinical diagnosis of type 2 diabetes and taking at least an oral or non-insulin injectable hypoglycemic agent and/or insulin).

The primary analysis compared the seroprotection rate at Week 28 for HEPLISAV-B (n= 640) with that at Week 28 for Engerix-B (n= 321) in subjects with type 2 diabetes mellitus. Non-inferiority of the seroprotection rate induced by HEPLISAV-B compared to Engerix-B was demonstrated (Table 5).

 | Table 5 Study 3: Seroprotection Rate of HEPLISAV-B and Engerix-B (subjects with type 2 diabetes mellitus ages 18 through 70 years)
Timepoint | HEPLISAV-B N = 640 | Engerix-B N = 321 | Difference in SPRs (HEPLISAV-B minus Engerix-B)
 | SPR (95% CI) | SPR (95% CI) | Difference (95% CI)
Week 28 | 90.0% (87.4, 92.2) | 65.1% (59.6, 70.3) | 24.9% (19.3, 30.7) [Noninferiority was met because the lower bound of the 95% confidence interval of the difference in SPRs was greater than -10%.]
CI = confidence interval; N = number of subjects in the analysis population in the group; SPR = seroprotection rate (% with anti-HBs ≥ 10 mIU/mL).
The SPR following HEPLISAV-B was statistically significantly higher than following Engerix-B (lower bound of the 95% confidence interval of the difference in SPRs was greater than 0%).
Clinical trial number: NCT02117934

A secondary analysis compared the seroprotection rate at Week 24 for HEPLISAV-B with that at Week 28 for Engerix-B in the total study population. Non-inferiority of the seroprotection rate induced by HEPLISAV-B compared to Engerix-B was demonstrated (Table 6).

 | Table 6 Study 3: Seroprotection Rate of HEPLISAV-B and Engerix-B (total study population ages 18 through 70 years)
Timepoint | HEPLISAV-B N = 4376 | Engerix-B N = 2289 | Difference in SPRs (HEPLISAV-B minus Engerix-B)
 | SPR (95% CI) | SPR (95% CI) | Difference (95% CI)
Week 24 (HEPLISAV-B) Week 28 (Engerix-B) | 95.4% (94.8, 96.0) | 81.3% (79.6, 82.8)) | 14.2% (12.5, 15.9) [Noninferiority was met because the lower bound of the 95% confidence interval of the difference in SPRs was greater than -10%.]
CI = confidence interval; N = number of subjects in the analysis population in the group; SPR = seroprotection rate (% with anti-HBs ≥ 10 mIU/mL).
Clinical trial number: NCT02117934
The SPR following HEPLISAV-B was statistically significantly higher than following Engerix-B (lower bound of the 95% confidence interval of the difference in SPRs was greater than 0%.).

Another secondary analysis compared the seroprotection rate at Week 24 for HEPLISAV-B with that at Week 28 for Engerix-B, by age group. For each age stratum non-inferiority of the seroprotection rate induced by HEPLISAV-B compared to Engerix-B was demonstrated (Table 7).

Age (years) | Table 7 Study 3: Seroprotection Rates of HEPLISAV-B and Engerix-B [Week 24 for HEPLISAV-B and Week 28 for Engerix-B] (ages 18 - 70 years)
Age (years) | HEPLISAV-B |  | Engerix-B |  | Difference in SPRs (HEPLISAV-B minus Engerix-B)
Age (years) | N | SPR (95% CI) | N | SPR (95% CI) | Difference (95% CI)
18-29 | 174 | 100.0% (97.9, 100.0) | 99 | 93.9% (87.3, 97.7) | 6.1% (2.8, 12.6) [Noninferiority was met because the lower bound of the 95% confidence interval of the difference in SPRs was greater than -10%.]
30-39 | 632 | 98.9% (97.7, 99.6) | 326 | 92.0% (88.5, 94.7) | 6.9% (4.2, 10.4)
40-49 | 974 | 97.2% (96.0, 98.2) | 518 | 84.2% (80.7, 87.2) | 13.1% (9.9, 16.6)
50-59 | 1439 | 95.2% (94.0, 96.3) | 758 | 79.7% (76.6, 82.5) | 15.5% (12.6, 18.7)
60-70 | 1157 | 91.6% (89.9, 93.1) | 588 | 72.6% (68.8, 76.2) | 19.0% (15.2, 23.0)
CI = confidence interval; N = number of subjects in the analysis population in the group; SPR = seroprotection rate (% with anti-HBs ≥ 10 mIU/mL).
Clinical trial number: NCT02117934
The SPR following HEPLISAV-B was statistically significantly higher than following Engerix-B (lower bound of the 95% confidence interval of the difference in SPRs was greater than 0%).

16 HOW SUPPLIED/STORAGE AND HANDLING

16.1 How Supplied

- Prefilled syringe, 1 dose (0.5 mL) - (NDC number: 43528-003-01)
- Package of 5 single dose prefilled syringes - (NDC number: 43528-003-05)

The tip caps and stoppers of the prefilled syringes are not made with natural rubber latex.

16.2 Storage Conditions

Store in a refrigerator at 2°C to 8°C (36°F to 46°F).
Do not freeze; discard if the vaccine has been frozen.
Do not use the vaccine after the expiration date shown on the prefilled syringe label.

17 PATIENT COUNSELING INFORMATION

- Inform vaccine recipient of the potential benefits and risks associated with vaccination, as well as the importance of completing the immunization series.
- Emphasize that HEPLISAV-B contains non-infectious purified HBsAg and cannot cause hepatitis B infection.
- Advise vaccine recipient to report any adverse events to their healthcare provider or to the Vaccine Adverse Event Reporting System (VAERS) at 1-800-822-7967 and www.vaers.hhs.gov.
- Provide the Vaccine Information Statements, which are available free of charge at the Centers for Disease Control and Prevention (CDC) website (www.cdc.gov/vaccines).

DYNAVAX

© 2017 - 2024, Dynavax Technologies Corporation.
All rights reserved.

Manufactured by:
Dynavax Technologies Corporation
Emeryville, CA 94608 USA

HVRA001 R05 09/24

PACKAGE LABEL

Principal Panel - Carton - Vials

Rx only

Hepatitis B Vaccine
(Recombinant),
Adjuvanted

HEPLISAV-B™

NDC 43528-002-05

5 x 0.5 mL
single-dose vials

For intramuscular
administration only

DYNAVAX

PACKAGE LABEL

Principal Panel - Carton - Prefilled Syringes

NDC 43528-003-05 Rx only

Hepatitis B Vaccine
(Recombinant),
Adjuvanted

HEPLISAV-B®

5 x 0.5 mL single-dose syringes

For intramuscular
administration only

For Adult Use Only

NEEDLES NOT INCLUDED

DYNAVAX

Principal Panel - Label - Prefilled Syringes

HEPLISAV-B®

1 dose (0.5 mL)

Hepatitis B Vaccine
(Recombinant), Adjuvanted

NDC 43528-003-01 Rx only
For IM use only DO NOT FREEZE
Store at 2-8°C (36-46°F)
Mfd. by Dynavax Tech. Corp.